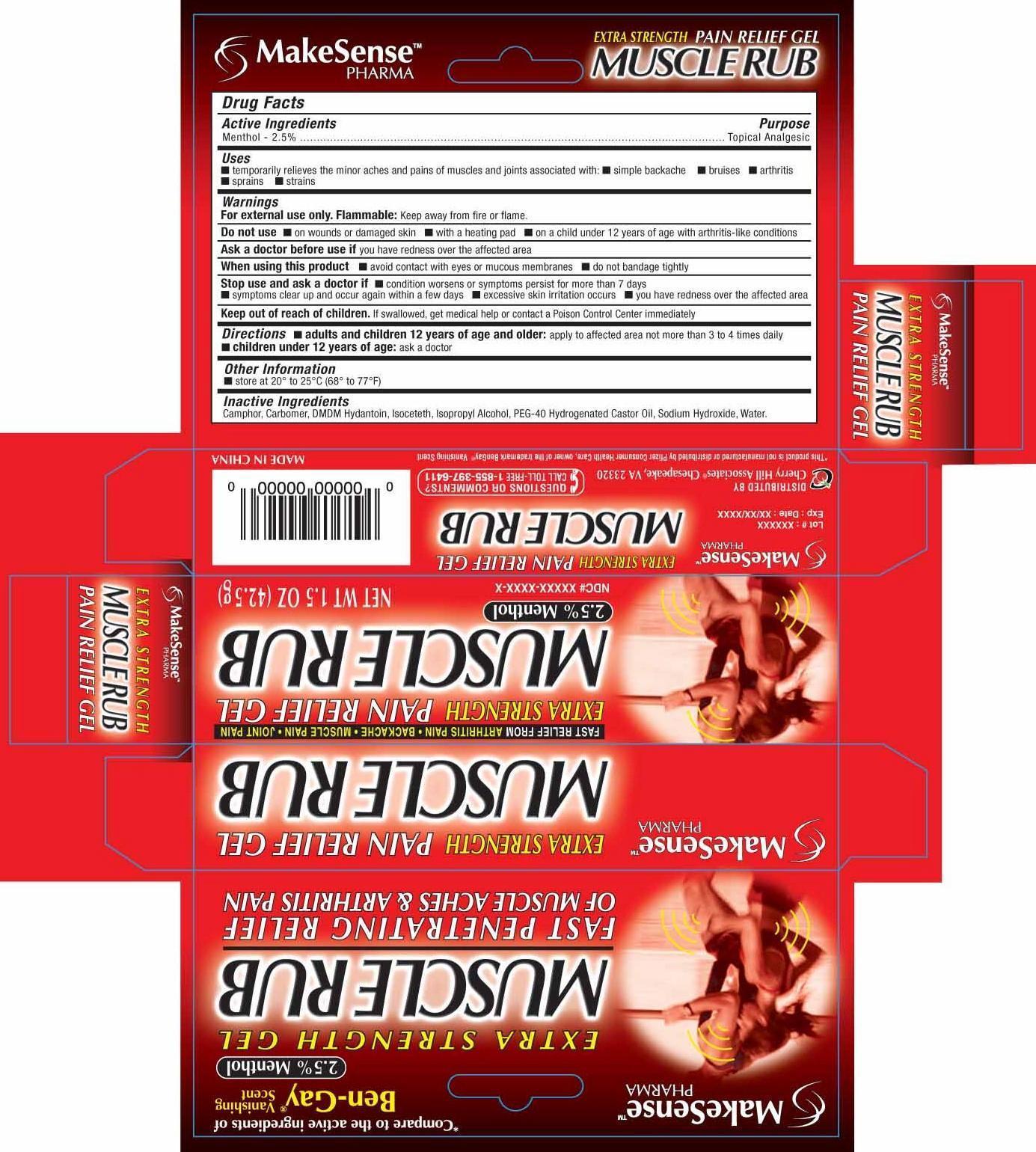 DRUG LABEL: MakeSense
NDC: 69020-200 | Form: GEL
Manufacturer: Cherry Hill Sales Co
Category: otc | Type: HUMAN OTC DRUG LABEL
Date: 20140613

ACTIVE INGREDIENTS: MENTHOL 2.5 g/100 g
INACTIVE INGREDIENTS: CAMPHOR (SYNTHETIC); DMDM HYDANTOIN; ISOPROPYL ALCOHOL; POLYOXYL 40 HYDROGENATED CASTOR OIL; SODIUM HYDROXIDE; WATER

Drug Facts

Active Ingredients

Menthol 2.5%

Purpose

Topical Analgesic

Uses

■ temporarily relieves the minor arthritis pains of muscles and joints associated with ■ simple backache ■ bruises ■arthritis ■strains ■sprains

Warnings

For external use only. Flammable: Keep away from fire or flame

Do not use

■ on wounds or damaged skin ■ with a heating pad ■ on a child under 12 years of age with arthritis like conditions

Ask a doctor before use

■ if you have redness over the affected area

When using this product

■ avoid contact with eyes or mucous membranes. ■ do not bandage tightly

Stop use and ask a doctor if

■ condition worsens, or symptoms persist for more than 7 days ■ symptoms clear-up and occur again within a few days, ■excessive skin irritation occurs ■ you have redness over the affected area

Keep out of reach of children

If swallowed, get medical help or contact a Poison Control Center right away

Directions

■ adults and children12 years of age and older: apply to affected area not more than 3-4 times

■ children under 12 years of age: ask a doctor

Other information

■ store at room temperature 20 to 25C (68 to 77F)

Inactive Ingredients

Camphor, Carbomer, DMDM Hydantoin, Isoceteth, Isopropyl Alcohol, PEG-40 Hydrogenated Castor Oil, Sodium Hydroxide and Water